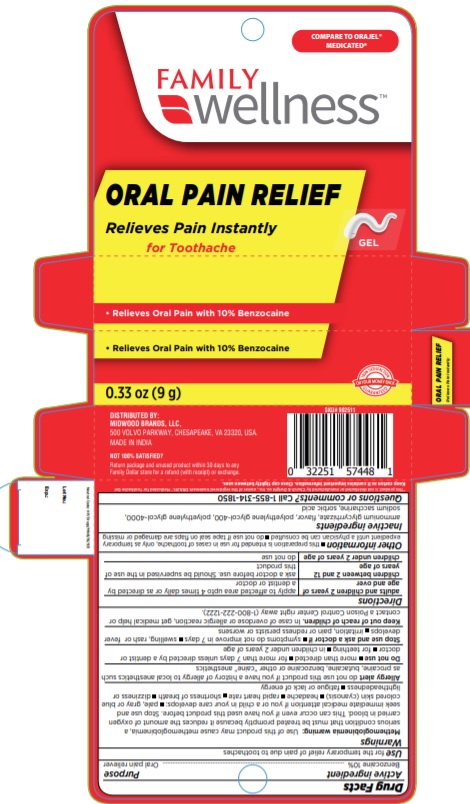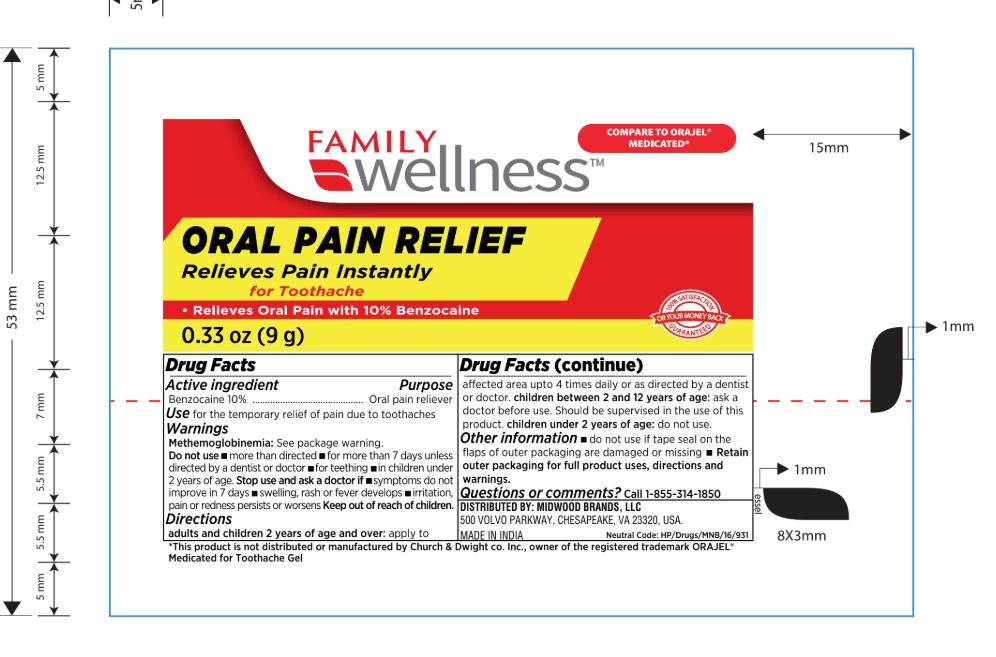 DRUG LABEL: Family wellness
NDC: 76168-607 | Form: GEL
Manufacturer: Velocity Pharma LLC
Category: otc | Type: HUMAN OTC DRUG LABEL
Date: 20200702

ACTIVE INGREDIENTS: BENZOCAINE 100 mg/1 g
INACTIVE INGREDIENTS: AMMONIUM GLYCYRRHIZATE; POLYETHYLENE GLYCOL 1000; SACCHARIN SODIUM; SORBIC ACID

Family wellness oral pain relief gel

Active ingredient

Benzocaine 10%

Purpose

Oral pain reliever

Use

- for the temporary relief of pain due to toothaches

Warnings

Methemoglobinemla: see package warning.

Do not use

- more than directed
- for more than 7 days unless directed by a physician or healthcare provider
- For teething
- in children under 2 year of age.

Stop use and ask a physician if

- swelling, rash or fever develops
- irritation, pain or redness persists or worsens
- symptoms do not improve in 7 days

KEEP OUT OF REACH OF CHILDREN:

In case of overdose or allergic reaction, get medical help or contact a Poison Control Center right away

DOSAGE AND ADMINISTRATION

Directions - cut open tip of tube on score mark

- Adults and children 2 years of age and over - Apply a samll amount of product to the cavity and around gum surrounding the teeth. Use up to 4 times daily or as directed by a physician or healthcare provider
- Children between 2 and 12 years of age - Should be supervised in the use of this product
- Children under 2 years of age - Ask a physicaian or healthcare provider

Other information

- do not use if tape seal on the flaps of outer packaging are damaged or miissing
- Retain outer packaging for full product uses,directions and warnings.

Inactive ingredients

ammonium glycyrrhizate, flavor, polyethylene glycol, sodium saccharin, sorbic acid